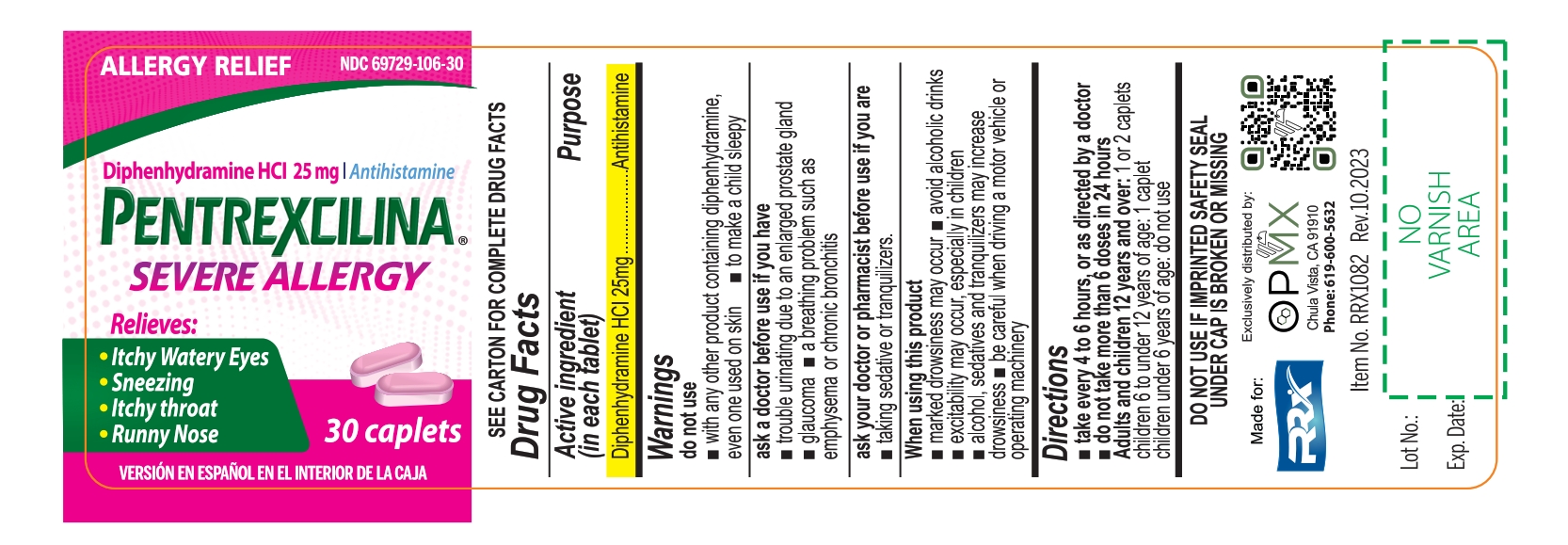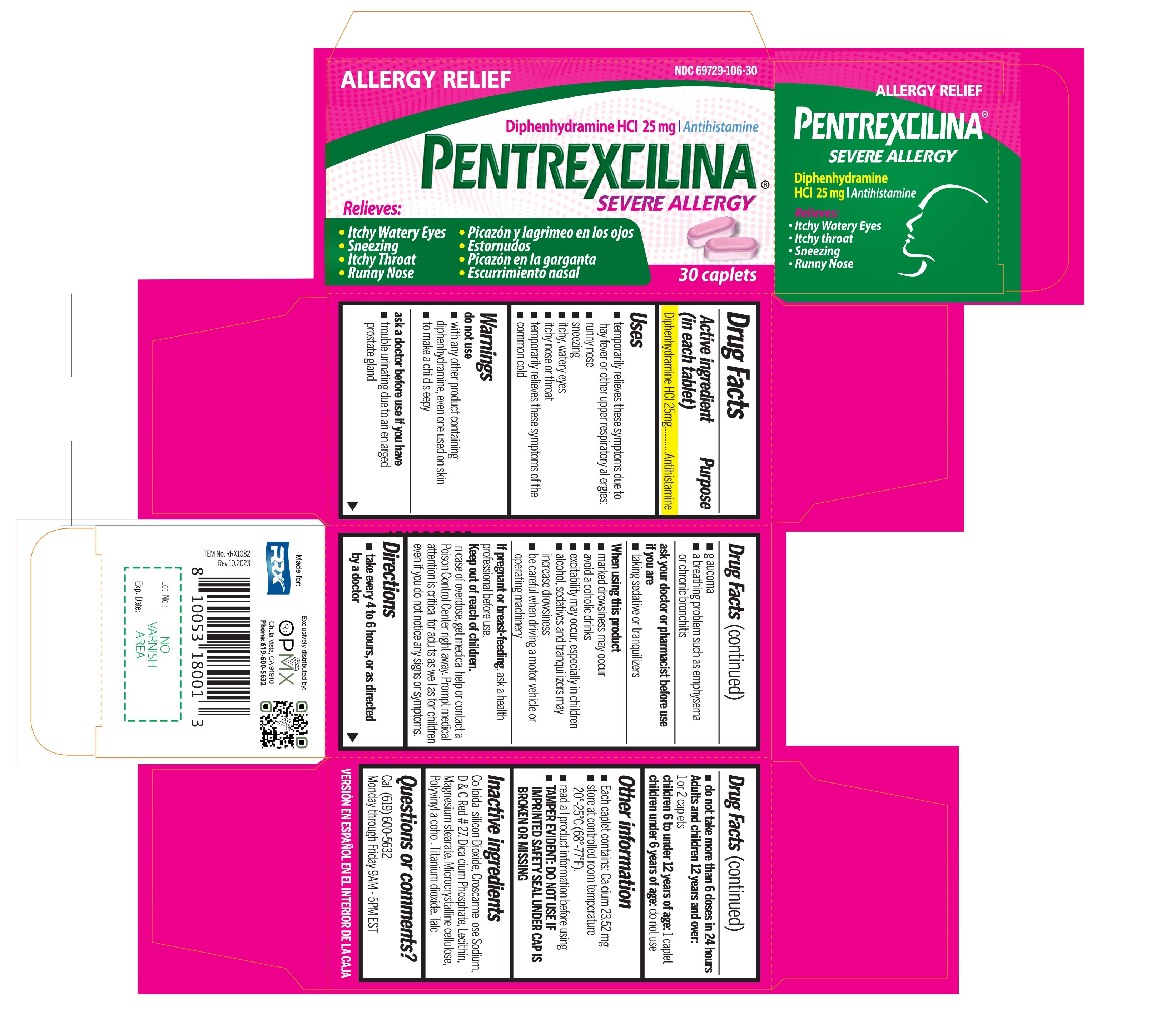 DRUG LABEL: Pentrexcilina Severe Allergy
NDC: 69729-106 | Form: TABLET, FILM COATED
Manufacturer: OPMX LLC
Category: otc | Type: HUMAN OTC DRUG LABEL
Date: 20240517

ACTIVE INGREDIENTS: DIPHENHYDRAMINE HYDROCHLORIDE 25 mg/1 1
INACTIVE INGREDIENTS: SILICON DIOXIDE; CROSCARMELLOSE SODIUM; D&C RED NO. 27; ANHYDROUS DIBASIC CALCIUM PHOSPHATE; LECITHIN, SOYBEAN; MAGNESIUM STEARATE; MICROCRYSTALLINE CELLULOSE; POLYVINYL ALCOHOL, UNSPECIFIED; TITANIUM DIOXIDE; TALC

Pentrexcilina Severe Allergy

Drug Facts

Active ingredient

Diphenhydramine HCl 25 mg

Purpose

Active ingredient (in each tablet) | Purpose
Diphenhydramine HCl 25mg | Antihistamine

Uses

- temporarily relieves these symptoms due to hay fever or other upper respiratory allergies:
  - runny nose
  - sneezing
  - itchy, watery eyes
  - itching of the nose or throat
- temporarily relieves these symptoms due to the common cold.

Warnings

Do not use

- with any other product containing diphenhydramine, even one used on skin
- to make a child sleepy

Ask a doctor before use if you have

- trouble urinating due to an enlarged prostate gland
- a breathing problem such as emphysema or chronic bronchitis
- glaucoma

Ask a doctor or pharmacist before use if you are, taking sedatives or tranquilizers

When using this product

- marked drowsiness may occur
- avoid alcoholic drinks
- excitability may occur, especially in children
- alcohol, sedatives, and tranquilizers may increase drowsiness
- be careful when driving a motor vehicle or operating machinery

PREGNANCY OR BREAST FEEDING

If pregnant or breast-feeding,ask a health professional before use.

Keep out of reach of children. In case of overdose, get medical help or contact a Poison Control Center right away. Prompt medical attention is critical for adults as well as for children even if you not notice ant signs or symptoms.

Directions

- take every 4 to 6 hours, or as directed by a doctor
- do not take more than 6 doses in 24 hours

adults and children 12 years and over | 1 or 2 caplets
children 6 to under 12 years | 1 caplet
children under 6 years | do not use

Other information

- each tablet contains:calcium 23.52 mg
- store at controlled room temperature 20-25°C (68-77°F).
- read all product information before using
- Tamper Evident: Do not use if imprinted safety seal under cap is broken or missing

Inactive ingredients

Colloidal silicon dioxide, Croscarmellose Sodium, D&C red no. 27 aluminum lake, dicalcium phosphate, lecithin, magnesium stearate, microcrystalline cellulose, polyvinyl alcohol, titanium dioxide, talc

Questions or comments?

call (619) 600-5632

Monday through Friday 9AM - 5PM EST

PRINCIPAL DISPLAY PANEL

NDC 69729-106-30

Diphenhydramine HCL 25mg/Antihistamine

Pentrexcilina®

SEVERE ALLERGY

Itchy, Watery Eyes - Picazón y lagrimeo en los ojos

Sneezing - Estornudo

Itchy Throat - Picazón en la garganta

Runny Nose - Escurrimiento Nasal

30 CAPLETS